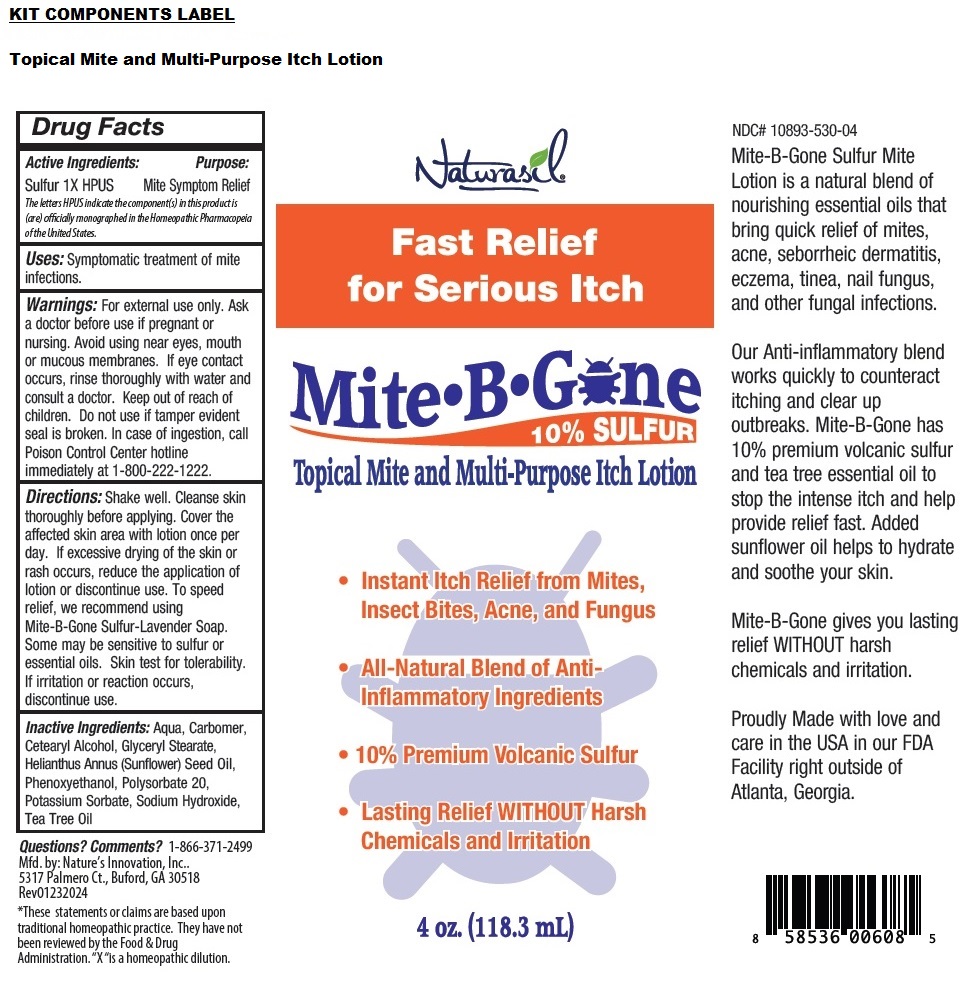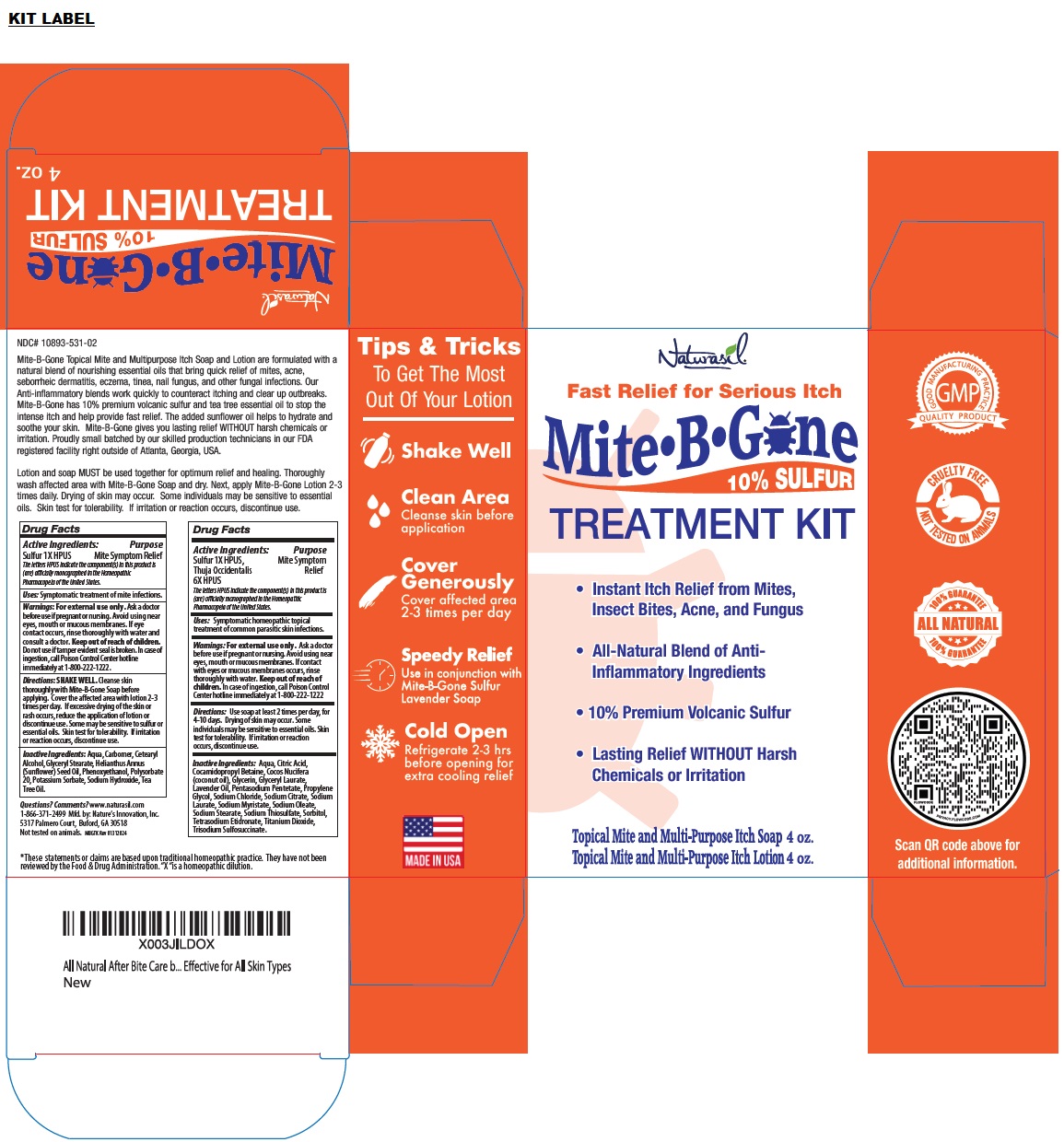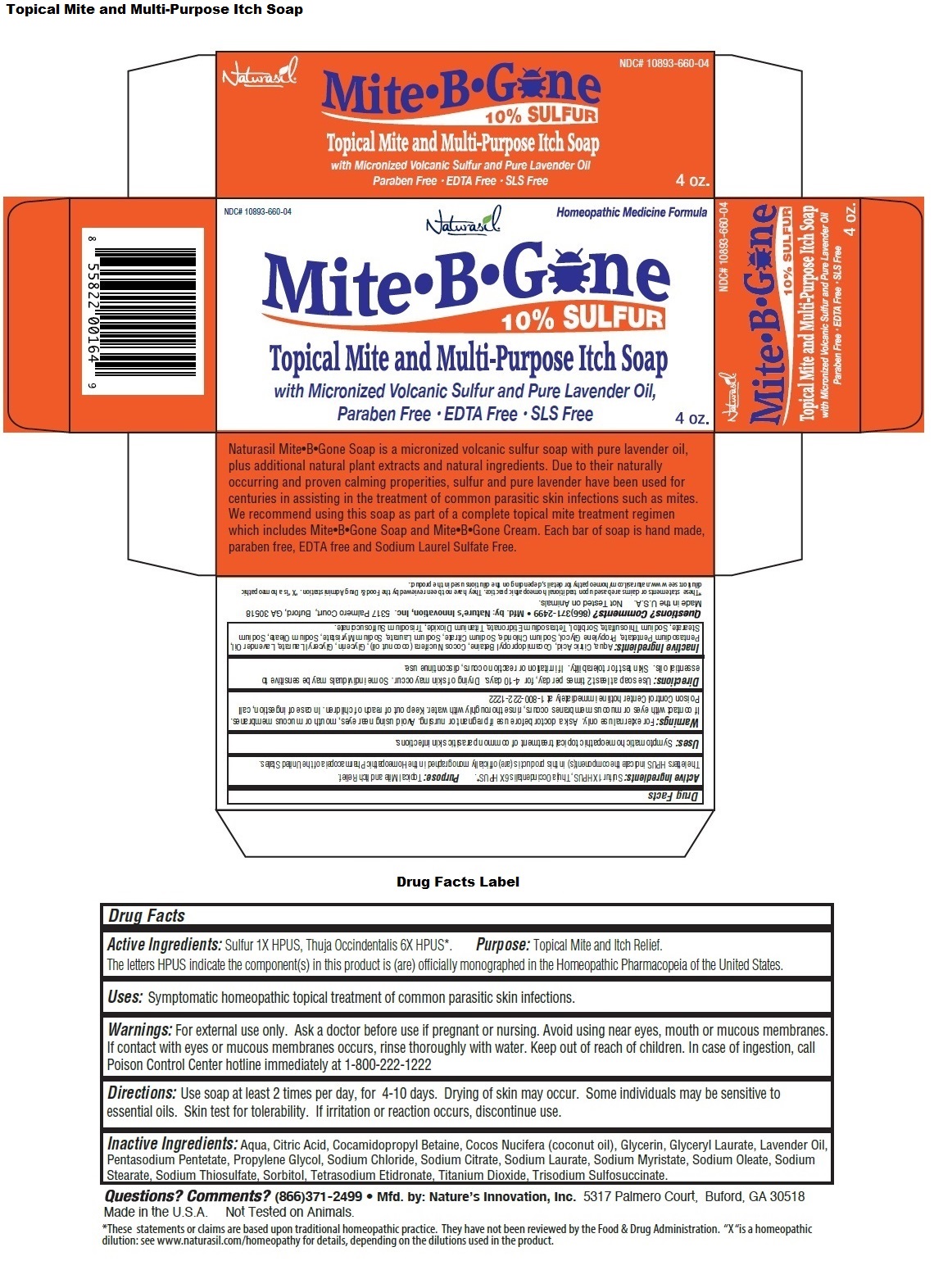 DRUG LABEL: Naturasil Mite B Gone TREATMENT Kit
NDC: 10893-531 | Form: KIT | Route: TOPICAL
Manufacturer: Nature's Innovation, Inc.
Category: homeopathic | Type: HUMAN OTC DRUG LABEL
Date: 20240207

ACTIVE INGREDIENTS: SULFUR 1 [hp_X]/118.3 mL; SULFUR 1 [hp_X]/113.3 g; THUJA OCCIDENTALIS LEAF 6 [hp_X]/113.3 g
INACTIVE INGREDIENTS: WATER; CARBOMER HOMOPOLYMER, UNSPECIFIED TYPE; CETOSTEARYL ALCOHOL; GLYCERYL MONOSTEARATE; SUNFLOWER OIL; PHENOXYETHANOL; POLYSORBATE 20; POTASSIUM SORBATE; SODIUM HYDROXIDE; TEA TREE OIL; WATER; CITRIC ACID MONOHYDRATE; COCAMIDOPROPYL BETAINE; COCONUT OIL; GLYCERIN; GLYCERYL LAURATE; LAVENDER OIL; PENTASODIUM PENTETATE; PROPYLENE GLYCOL; SODIUM CHLORIDE; SODIUM CITRATE, UNSPECIFIED FORM; SODIUM LAURATE; SODIUM MYRISTATE; SODIUM OLEATE; SODIUM STEARATE; SODIUM THIOSULFATE; SORBITOL; ETIDRONATE TETRASODIUM; TITANIUM DIOXIDE; TRISODIUM SULFOSUCCINATE

Naturasil® Mite• B• Gone TREATMENT KIT

Topical Mite and Multi-Purpose Itch Lotion

Drug Facts

Active Ingredients:

Sulfur 1X HPUS

The letters HPUS indicate the component(s) in this product is (are) officially monographed in the Homeopathic Pharmacopeia of the United States.

Purpose

Mite Symptom Relief

INDICATIONS AND USAGE

Uses: Symptomatic treatment of mite infections.

WARNINGS

Warnings: For external use only. Ask a doctor before use if pregnant or nursing. Avoid using near eyes, mouth or mucous membranes. If eye contact occurs, rinse thoroughly with water and consult a doctor.

Keep out of reach of children. Do not use if tamper evident seal is broken. In case of ingestion, call Poison Control Center hotline immediately at 1-800-222-1222.

DOSAGE AND ADMINISTRATION

Directions: SHAKE WELL. Cleanse skin thoroughly with Mite-B-Gone Soap before applying. Cover the affected area with lotion 2-3 times per day. If excessive drying of the skin or rash occurs, reduce the application of lotion or discontinue use. Some may be sensitive to sulfur or essential oils. Skin test for tolerability. If irritation or reaction occurs, discontinue use.

INACTIVE INGREDIENT

Inactive Ingredients: Aqua, Carbomer, Cetearyl Alcohol, Glyceryl Stearate, Helianthus Annus (Sunflower) Seed Oil, Phenoxyethanol, Polysorbate 20, Potassium Sorbate, Sodium Hydroxide, Tea Tree Oil.

Topical Mite and Multi-Purpose Itch Soap

Drug Facts

Active Ingredients:

Sulfur 1X HPUS, Thuja Occidentalis 6X HPUS

The letters HPUS indicate the component(s) in this product is (are) officially monographed in the Homeopathic Pharmacopeia of the United States.

Purpose

Mite Symptom Relief

INDICATIONS AND USAGE

Uses: Symptomatic homeopathic topical treatment of common parasitic skin infections.

WARNINGS

Warnings: For external use only. Ask a doctor before use if pregnant or nursing. Avoid using near eyes, mouth or mucous membranes. If contact with eyes or mucous membranes occurs, rinse thoroughly with water.

Keep out of reach of children. In case of ingestion, call Poison Control Center hotline immediately at 1-800-222-1222

DOSAGE AND ADMINISTRATION

Directions: Use soap at least 2 times per day, for 4-10 days. Drying of skin may occur. Some individuals may be sensitive to essential oils. Skin test for tolerability. If irritation or reaction occurs, discontinue use.

INACTIVE INGREDIENT

Inactive Ingredients: Aqua, Citric Acid, Cocamidopropyl Betaine, Cocos Nucifera (coconut oil), Glycerin, Glyceryl Laurate, Lavender Oil, Pentasodium Pentetate, Propylene Glycol, Sodium Chloride, Sodium Citrate, Sodium Laurate, Sodium Myristate, Sodium Oleate, Sodium Stearate, Sodium Thiosulfate, Sorbitol, Tetrasodium Etidronate, Titanium Dioxide, Trisodium Sulfosuccinate.

Fast Relief for Serious Itch

10% SULFUR

• Instant Itch Relief from Mites, Insect Bites, Acne, and Fungus
• All-Natural Blend of Anti-Inflammatory Ingredients
• 10% Premium Volcanic Sulfur
• Lasting Relief WITHOUT Harsh Chemicals or Irritation

GOOD MANUFACTURING PRACTICE
QUALITY PRODUCT

CRUELTY FREE
NOT TESTED ON ANIMALS

ALL NATURAL 100% GUARANTEE

Mite-B-Gone Topical Mite and Multipurpose Itch Soap and Lotion are formulated with a natural blend of nourishing essential oils that bring quick relief of mites, acne, seborrheic dermatitis, eczema, tinea, nail fungus, and other fungal infections. Our Anti-inflammatory blends work quickly to counteract itching and clear up outbreaks. Mite-B-Gone has 10% premium volcanic sulfur and tea tree essential oil to stop the intense itch and help provide fast relief. The added sunflower oil helps to hydrate and soothe your skin. Mite-B-Gone gives you lasting relief WITHOUT harsh chemicals or irritation. Proudly small batched by our skilled production technicians in our FDA registered facility right outside of Atlanta, Georgia, USA.

Lotion and soap MUST be used together for optimum relief and healing. Thoroughly wash affected area with Mite-B-Gone Soap and dry. Next, apply Mite-B-Gone Lotion 2-3 times daily. Drying of skin may occur. Some individuals may be sensitive to essential oils. Skin test for tolerability. If irritation or reaction occurs, discontinue use.

Questions? Comments? www.naturasil.com
1-866-371-2499 Mfd. by: Nature’s Innovation, Inc.
5317 Palmero Court, Buford, GA 30518

*These statements or claims are based upon traditional homeopathic practice. They have not been reviewed by the Food & Drug Administration. “X “is a homeopathic dilution.

Tips & Tricks
To Get The Most Out Of Your Lotion

Shake Well

Clean Area
Cleanse skin before application

Cover Generously
Cover affected area 2-3 times per day

Speedy Relief
Use in conjunction with Mite-B-Gone Sulfur Lavender Soap

Cold Open
Refrigerate 2-3 hrs before opening for extra cooling relief

MADE IN USA